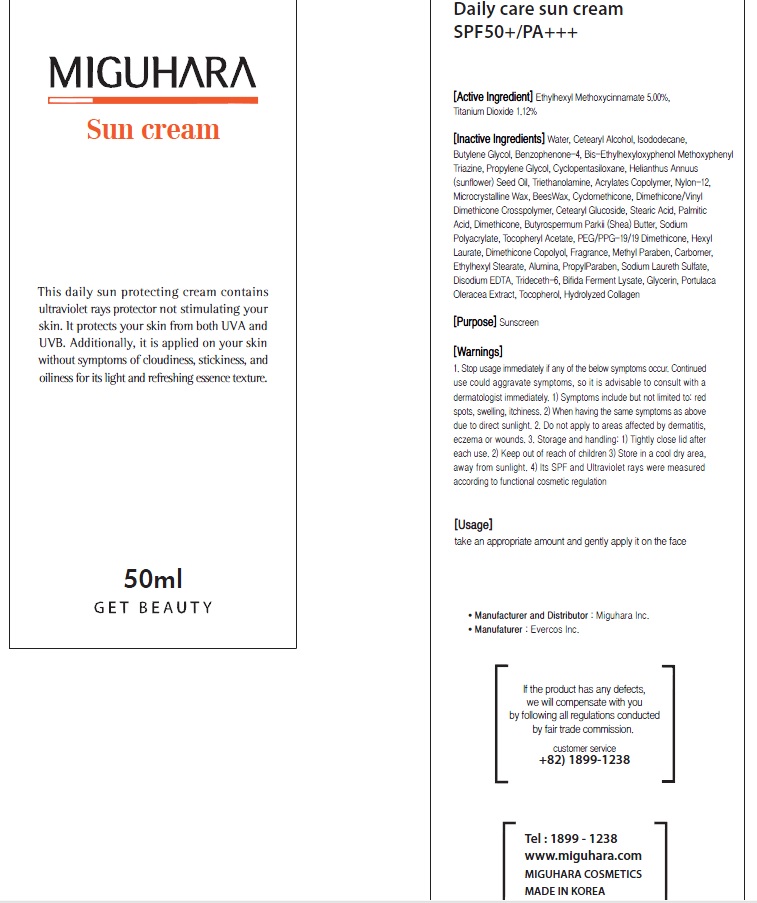 DRUG LABEL: Daily Care Sun
NDC: 70380-160 | Form: CREAM
Manufacturer: MIGUHARA
Category: otc | Type: HUMAN OTC DRUG LABEL
Date: 20160222

ACTIVE INGREDIENTS: Octinoxate 2.50 g/50 mL; Titanium Dioxide 0.56 g/50 mL
INACTIVE INGREDIENTS: Water; Isododecane

ACTIVE INGREDIENT

Active Ingredient: Ethylhexyl Methoxycinnamate 5.00%, Titanium Dioxide 1.12%

INACTIVE INGREDIENT

Inactive Ingredients: Water, Cetearyl Alcohol, Isododecane, Butylene Glycol, Benzophenone-4, Bis-Ethylhexyloxyphenol Methoxyphenyl Triazine, Propylene Glycol, Cyclopentasiloxane, Helianthus Annuus (sunflower) Seed Oil, Triethanolamine, Acrylates Copolymer, Nylon-12, Microcrystalline Wax, BeesWax, Cyclomethicone, Dimethicone/Vinyl Dimethicone Crosspolymer, Cetearyl Glucoside, Stearic Acid, Palmitic Acid, Dimethicone, Butyrospermum Parkii (Shea) Butter, Sodium Polyacrylate, Tocopheryl Acetate, PEG/PPG-19/19 Dimethicone, Hexyl Laurate, Dimethicone Copolyol, Fragrance, Methyl Paraben, Carbomer, Ethylhexyl Stearate, Alumina, PropylParaben, Sodium Laureth Sulfate, Disodium EDTA, Trideceth-6, Bifida Ferment Lysate, Glycerin, Portulaca Oleracea Extract, Tocopherol, Hydrolyzed Collagen

PURPOSE

Purpose: Sunscreen

WARNINGS

1. Stop usage immediately if any of the below symptoms occur. Continued use could aggravate symptoms, so it is advisable to consult with a dermatologist immediately. 1) Symptoms include but not limited to: red spots, swelling, itchiness. 2) When having the same symptoms as above due to direct sunlight. 2. Do not apply to areas affected by dermatitis, eczema or wounds. 3. Storage and handling: 1) Tightly close lid after each use. 2 Keep out of reach of children 3) Store in a cool dry area, away from sunlight 4) Its SPF and Ultraviolet rays were measured according to functional cosmetic regulation.

Usage

Usage: Take an appropriate amount and gently apply it on the face.